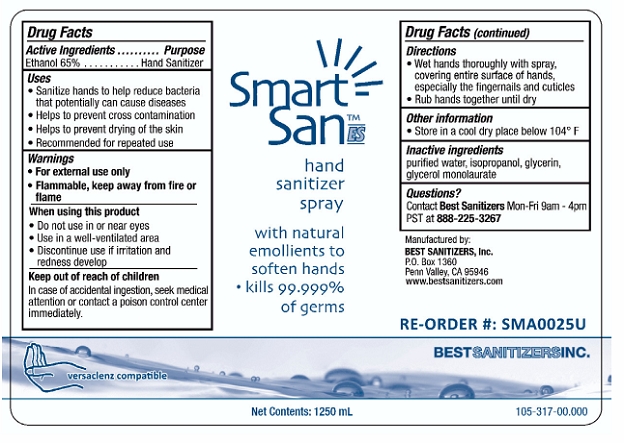 DRUG LABEL: Smart San ES Hand Sanitizer Spray
NDC: 59900-114 | Form: LIQUID
Manufacturer: Best Sanitizers, Inc
Category: otc | Type: HUMAN OTC DRUG LABEL
Date: 20100305

ACTIVE INGREDIENTS: Ethanol 652.2 g/1000 mL

Drug Facts

Active Ingredient

Ethanol 65%

Purpose

Hand Sanitizer

Uses

- Sanitize Hands to help reduce bacteria that potentially can causes disease
- Helps to prevent cross contamination
- Helps to prevent drying of the skin
- Recommended for repeated use

Warnings

- For external use only
- Flammable, keep away from fire or flame

When Using this product

- Do not use in or near eyes
- Use in a well-ventilated area
- Discontinue use if irritation and redness develop

Keep out of reach of children

In case of accidental ingestion, seek medical attention or contact a poison control center immediately.

Directions

- Wet hands thoroughly with spray, covering entire surface of hands, especially the fingernails and cuticles
- Rub hands together until dry

Other information

Store in a cool dry place below 104° F

Inactive ingredients

purified water, isopropanol, glycerin, glycerol monolaurate

Questions?

Contact Best Sanitizers Mon-Fri 9am-4pm PST at 888-225-3267

Principal Display Panel

NDC 59900-114-02

NDC 59900-114-03

NDC 59900-114-04

NDC 59900-114-05

NDC 59900-114-06

Smart San™ ES

hand sanitizer spray

with natural emollients to soften hands

- kills 99.999% of germs